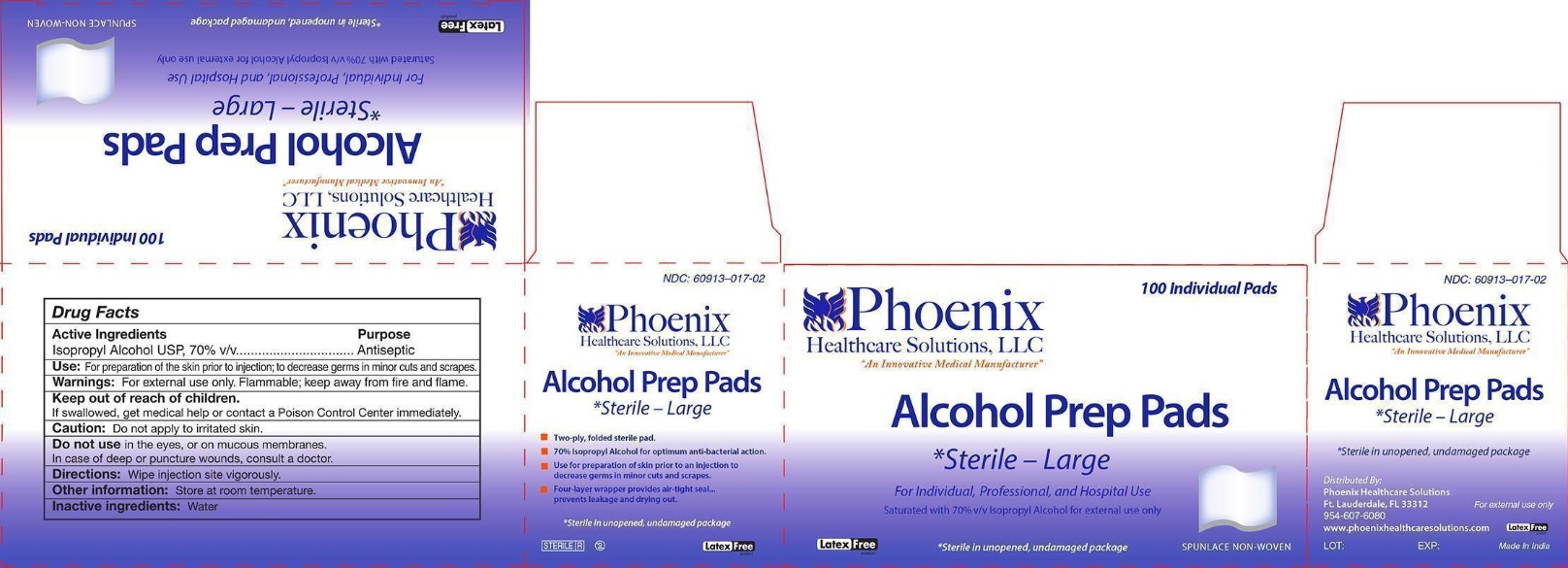 DRUG LABEL: Alcohol Prep
NDC: 60913-017 | Form: SWAB
Manufacturer: PHOENIX HEALTHCARE SOLUTIONS, LLC
Category: otc | Type: HUMAN OTC DRUG LABEL
Date: 20251023

ACTIVE INGREDIENTS: ISOPROPYL ALCOHOL 70 mL/100 mL
INACTIVE INGREDIENTS: WATER

Phoenix Alcohol Prep Pad

Active Ingredients

Isopropyl alcohol 70% v/v

Purpose

Antiseptic

Use:

For preparation of the skin prior to injection; to decrease germs in minor cuts and scrapes.

Warnings:

- For external use only. Flammable; keep away from fire and flame.

Keep out of reach of children.

If swallowed, get medical help or contact a Poison Control Center immediately.

Caution:

Do not apply to irritated skin.

Do not use

in the eyes, or on mucous membranes. In case of deep or puncture wounds, consult a doctor.

Directions:

Wipe injection site vigorously.

Other information:

Store at room temperature

Inactive ingredients:

Water

Principal Display Panel

NDC 60913-017-02

Phoenix Healthcare Solutions,LLC

"An Innovative Medical Manufacturer"

100 Individual Pads

Alcohol Prep Pads

*Sterile - Large

For Individual, Professional and Hospital Use

Saturated with 70% v/v Isopropyl Alcohol for external use only

Latex Free

*Sterile in unopened, undamaged package

SPUNLACE NON-WOVEN